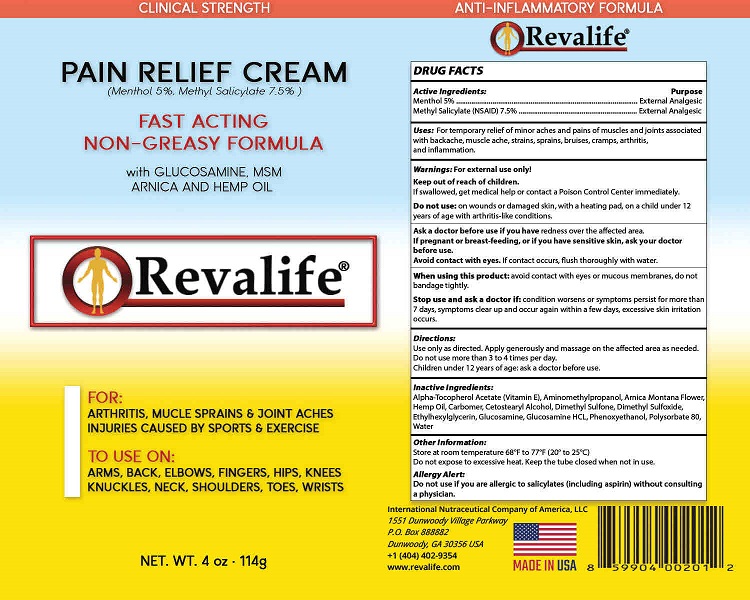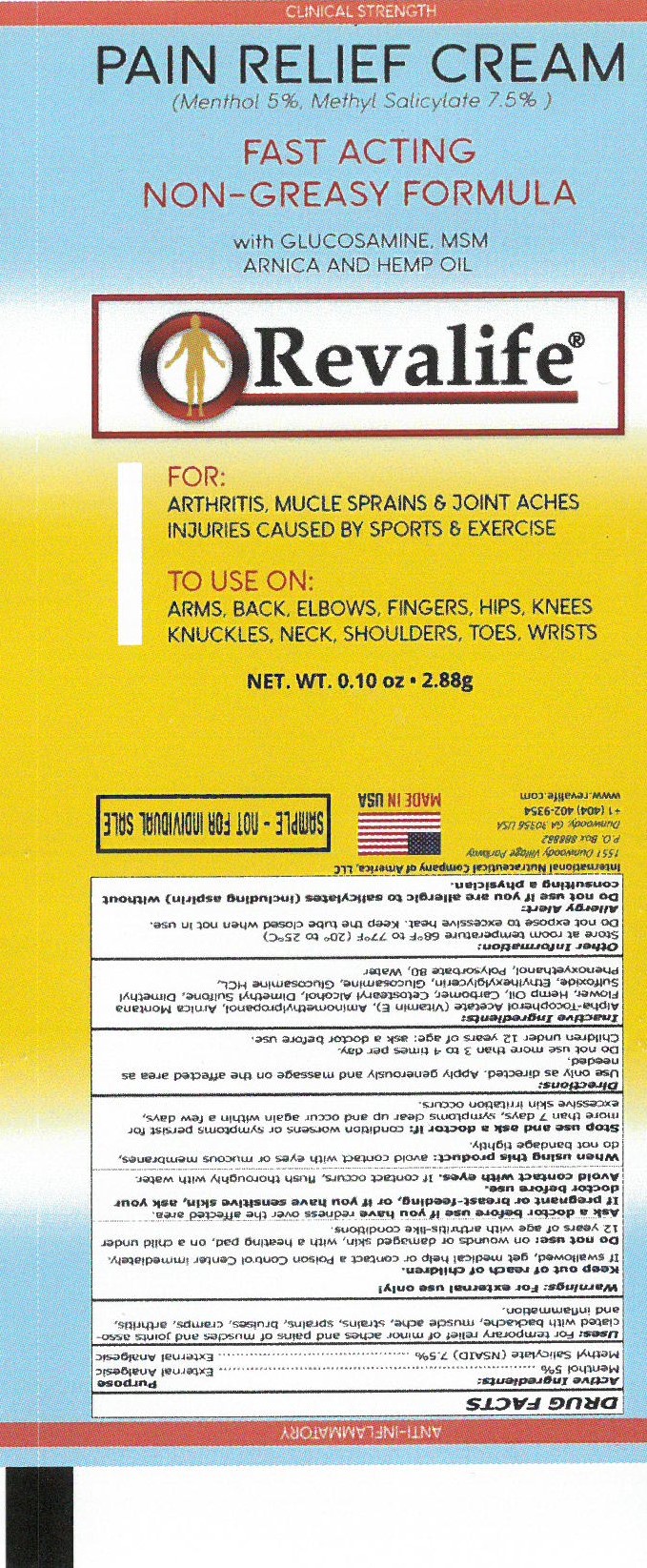 DRUG LABEL: Revalife Pain Relief Cream
NDC: 42452-379 | Form: CREAM
Manufacturer: International Nutraceutical Company of America, LLC
Category: otc | Type: HUMAN OTC DRUG LABEL
Date: 20220214

ACTIVE INGREDIENTS: MENTHOL 0.05 kg/1 kg; METHYL SALICYLATE 0.075 kg/1 kg
INACTIVE INGREDIENTS: WATER; CARBOMER HOMOPOLYMER TYPE C; DIMETHYL SULFONE; DIMETHYL SULFOXIDE; N-ACETYLGLUCOSAMINE; GLUCOSAMINE HYDROCHLORIDE; GLYCERYL STEARATE SE; Polysorbate 80; CETOSTEARYL ALCOHOL; ARNICA MONTANA; CANNABIS SATIVA SEED OIL; COCONUT OIL; .ALPHA.-TOCOPHEROL ACETATE, DL-; PHENOXYETHANOL; ETHYLHEXYLGLYCERIN; MAGNESIUM HYDROXIDE; AMINOMETHYLPROPANOL

Revalife - Pain Relief Cream

DRUG FACTS

Menthol - 5% (External Analgesic)
Methyl Salicylate (NSAID) – 7.5% (External Analgesic)

Uses:

For temporary relief of minor aches and pains of muscles and joints associated with backache, muscle ache, strains, sprains, bruises, cramps, arthritis, and inflammation

Warnings:

External Use Only!

Keep out of reach of children.
If swallowed, get medical help or contact a Poison Control Center immediately.

Do not use:
• on wounds or damaged skin
• with a heating pad
• on a child under 12 years of age with arthritis-like conditions

Ask a doctor before use if you have redness over the affected area.

If pregnant or breast-feeding, or if you have sensitive skin, ask your doctor before use

Avoid contact with eyes. If contact occurs, flush thoroughly with water.

When using this product:
• avoid contact with eyes or mucous membranes
• do not bandage tightly

Stop use and ask a doctor if: condition worsens or symptoms persist for more than 7 days, symptoms clear up and occur again within a few days, excessive skin irritation occurs

Directions:

Use only as directed. Apply generously and massage to affected area as needed. Do not use more than 3 to 4 times per day.
Children under 12 years of age: ask a doctor before use.

Inactive Ingredients:

Alpha-Tocopherol Acetate (Vitamin E), Aminomethylpropanol, Arnica Montana Flower, Carbomer, Cetostearyl Alcohol, Coconut Oil, Dimethyl Sulfone, Dimethyl Sulfoxide, Ethylhexylglycerin, Glucosamine HCL, Glyceryl Monostearate, Hemp Oil, Magnesium Hydroxide, N-Acetyl Glucosamine, Phenoxyethanol, Polysorbate 80, Water

Other Information:

Store at room temperature 68°F to 77°F (20° to 25°C)
Do not expose to excessive heat

Allergy Alert:

Do not use if you are allergic to salicylates (including aspirin) without consulting a physician.

For Questions

International Neutraceutical Company of America, LLC

1551 Dunwoody Village Parkway

P.O. Box 888882

Dunwoody, GA 30356 USA

+1 (404) 402-9354

www.revalife.com